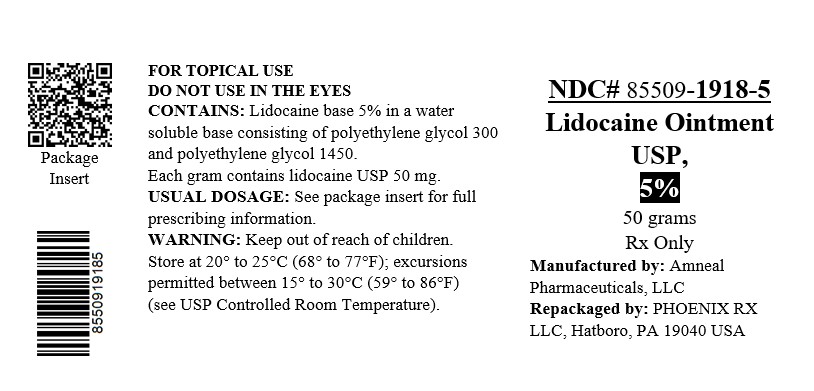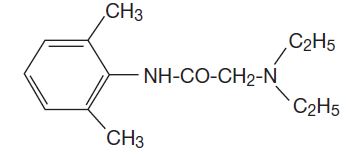 DRUG LABEL: Lidocaine
NDC: 85509-1918 | Form: OINTMENT
Manufacturer: PHOENIX RX LLC
Category: prescription | Type: HUMAN PRESCRIPTION DRUG LABEL
Date: 20260204

ACTIVE INGREDIENTS: LIDOCAINE 50 mg/1 g
INACTIVE INGREDIENTS: POLYETHYLENE GLYCOL, UNSPECIFIED

Lidocaine Ointment USP, 5%
FOR TOPICAL USE
DO NOT USE IN THE EYES
Rx Only

DESCRIPTION

Lidocaine Ointment USP, 5% contains a local anesthetic agent and is administered topically. See INDICATIONS AND USAGEfor specific uses.

Lidocaine Ointment USP, 5% contains lidocaine USP, which is chemically designated as acetamide, 2-(diethylamino)- N-(2,6-dimethylphenyl)-,and has the following structural formula:

Composition of Lidocaine Ointment USP, 5%: acetamide, 2-(diethylamino)- N-(2,6-dimethylphenyl)-, (lidocaine) 5% in a water miscible ointment vehicle containing polyethylene glycols.

CLINICAL PHARMACOLOGY

Mechanism of action

Lidocaine stabilizes the neuronal membrane by inhibiting the ionic fluxes required for the initiation and conduction of impulses, thereby effecting local anesthetic action.

Onset of anesthesia

Lidocaine Ointment 5% effects local, topical anesthesia. The onset of action is 3 to 5 minutes. It is ineffective when applied to intact skin.

Hemodynamics

Excessive blood levels may cause changes in cardiac output, total peripheral resistance, and mean arterial pressure. These changes may be attributable to a direct depressant effect of the local anesthetic agent on various components of the cardiovascular system.

Pharmacokinetics and metabolism

Lidocaine may be absorbed following topical administration to mucous membranes, its rate and extent of absorption depending upon the specific site of application, duration of exposure, concentration, and total dosage. In general, the rate of absorption of local anesthetic agents following topical application occurs most rapidly after intratracheal administration. Lidocaine is also well-absorbed from the gastrointestinal tract, but little intact drug appears in the circulation because of biotransformation in the liver.

Lidocaine is metabolized rapidly by the liver, and metabolites and unchanged drug are excreted by the kidneys. Biotransformation includes oxidative N-dealkylation, ring hydroxylation, cleavage of the amide linkage, and conjugation. N-dealkylation, a major pathway of biotransformation, yields the metabolites monoethylglycinexylidide and glycinexylidide. The pharmacological/toxicological actions of these metabolites are similar to, but less potent than, those of lidocaine. Approximately 90% of lidocaine administered is excreted in the form of various metabolites, and less than 10% is excreted unchanged. The primary metabolite in urine is a conjugate of 4-hydroxy-2,6-dimethylaniline.

The plasma binding of lidocaine is dependent on drug concentration, and the fraction bound decreases with increasing concentration. At concentrations of 1 to 4 mcg of free base per mL, 60 to 80 percent of lidocaine is protein bound. Binding is also dependent on the plasma concentration of the alpha-l-acid glycoprotein.

Lidocaine crosses the blood-brain and placental barriers, presumably by passive diffusion.

Studies of lidocaine metabolism following intravenous bolus injections have shown that the elimination half-life of this agent is typically 1.5 to 2 hours. Because of the rapid rate at which lidocaine is metabolized, any condition that affects liver function may alter lidocaine kinetics. The half-life may be prolonged two-fold or more in patients with liver dysfunction. Renal dysfunction does not affect lidocaine kinetics but may increase the accumulation of metabolites.

Factors such as acidosis and the use of CNS stimulants and depressants affect the CNS levels of lidocaine required to produce overt systemic effects. Objective adverse manifestations become increasingly apparent with increasing venous plasma levels above 6 mcg free base per mL. In the rhesus monkey arterial blood levels of 18 to 21 mcg/mL have been shown to be threshold for convulsive activity.

INDICATIONS AND USAGE

Lidocaine Ointment 5% is indicated for production of anesthesia of accessible mucous membranes of the oropharynx.

It is also useful as an anesthetic lubricant for intubation and for the temporary relief of pain associated with minor burns, including sunburn, abrasions of the skin, and insect bites.

CONTRAINDICATIONS

Lidocaine is contraindicated in patients with a known history of hypersensitivity to local anesthetics of the amide type or to other components of Lidocaine Ointment 5%.

WARNINGS

EXCESSIVE DOSAGE, OR SHORT INTERVALS BETWEEN DOSES, CAN RESULT IN HIGH PLASMA LEVELS AND SERIOUS ADVERSE EFFECTS, PATIENTS SHOULD BE INSTRUCTED TO STRICTLY ADHERE TO THE RECOMMENDED DOSAGE AND ADMINISTRATION GUIDELINES AS SET FORTH IN THIS PACKAGE INSERT.

THE MANAGEMENT OF SERIOUS ADVERSE REACTIONS MAY REQUIRE THE USE OF RESUSCITATIVE EQUIPMENT, OXYGEN, AND OTHER RESUSCITATIVE DRUGS.

Lidocaine Ointment 5% should be used with extreme caution in the presence of sepsis or severely traumatized mucosa in the area of application, since under such conditions there is the potential for rapid systemic absorption.

Methemoglobinemia

Cases of methemoglobinemia have been reported in association with local anesthetic use. Although all patients are at risk for methemoglobinemia, patients with glucose-6-phosphate dehydrogenase deficiency, congenital or idiopathic methemoglobinemia, cardiac or pulmonary compromise, infants under 6 months of age, and concurrent exposure to oxidizing agents or their metabolites are more susceptible to developing clinical manifestations of the condition. If local anesthetics must be used in these patients, close monitoring for symptoms and signs of methemoglobinemia is recommended.

Signs of methemoglobinemia may occur immediately or may be delayed some hours after exposure, and are characterized by a cyanotic skin discoloration and/or abnormal coloration of the blood. Methemoglobin levels may continue to rise; therefore, immediate treatment is required to avert more serious central nervous system and cardiovascular adverse effects, including seizures, coma, arrhythmias, and death. Discontinue Lidocaine Ointment 5% and any other oxidizing agents. Depending on the severity of the signs and symptoms, patients may respond to supportive care, i.e., oxygen therapy, hydration. A more severe clinical presentation may require treatment with methylene blue, exchange transfusion, or hyperbaric oxygen.

PRECAUTIONS

General

The safety and effectiveness of lidocaine depend on proper dosage, correct technique, adequate precautions, and readiness for emergencies (see WARNINGSand ADVERSE REACTIONS). The lowest dosage that results in effective anesthesia should be used to avoid high plasma levels and serious adverse effects. Repeated doses of lidocaine may cause significant increases in blood levels with each repeated dose because of slow accumulation of the drug and/or its metabolites. Tolerance to elevated blood levels varies with the status of the patient. Debilitated, elderly patients, acutely ill patients, and children should be given reduced doses commensurate with their age and physical condition. Lidocaine should also be used with caution in patients with severe shock or heart block.

Lidocaine Ointment 5% should be used with caution in patients with known drug sensitivities. Patients allergic to paraaminobenzoic acid derivatives (procaine, tetracaine, benzocaine, etc.) have not shown cross sensitivity to lidocaine. Many drugs used during the conduct of anesthesia are considered potential triggering agents for familial malignant hyperthermia. Since it is not known whether amide-type local anesthetics may trigger this reaction and since the need for supplemental general anesthesia cannot be predicted in advance, it is suggested that a standard protocol for the management of malignant hyperthermia should be available. Early unexplained signs of tachycardia, tachypnea, labile blood pressure and metabolic acidosis may precede temperature elevation. Successful outcome is dependent on early diagnosis, prompt discontinuance of the suspect triggering agent(s) and institution of treatment, including oxygen therapy, indicated supportive measures and dantrolene (consult dantrolene sodium intravenous package insert before using).

Drug Interactions

Patients who are administered local anesthetics are at increased risk of developing methemoglobinemia when concurrently exposed to the following drugs, which could include other local anesthetics:

Examples of Drugs Associated with Methemoglobinemia:

Class | Examples
Nitrates/Nitrites | nitroglycerin, nitroprusside, nitric oxide, nitrous oxide
Local anesthetics | benzocaine, lidocaine, bupivacaine, mepivacaine, tetracaine, prilocaine, procaine, articaine
Antineoplastic agents | cyclophosphamide, flutamide, rasburicase, ifosfamide, hydroxyurea
Antibiotics | dapsone, sulfonamides, nitrofurantoin, para-aminosalicylic acid
Antimalarials | chloroquine, primaquine
Anticonvulsants | phenytoin, sodium valproate, phenobarbital
Other drugs | acetaminophen, metoclopramide, sulfa drugs (i.e., sulfasalazine), quinine

Information for Patients

When topical anesthetics are used in the mouth, the patient should be aware that the production of topical anesthesia may impair swallowing and thus enhance the danger of aspiration. For this reason, food should not be ingested for 60 minutes following the use of local anesthetic preparations in the mouth or throat area. This is particularly important in children because of their frequency of eating.

Numbness of the tongue or buccal mucosa may enhance the danger of unintentional biting trauma. Food and chewing gum should not be taken while the mouth or throat area is anesthetized.

Inform patients that use of local anesthetics may cause methemoglobinemia, a serious condition that must be treated promptly. Advise patients or caregivers to seek immediate medical attention if they or someone in their care experience the following signs or symptoms: pale, gray, or blue colored skin (cyanosis); headache; rapid heart rate; shortness of breath; lightheadedness; or fatigue.

Carcinogenesis, Mutagenesis, Impairment of Fertility

Studies of lidocaine in animals to evaluate the carcinogenic and mutagenic potential or the effect on fertility have not been conducted.

Use in Pregnancy

Teratogenic Effects. Pregnancy Category B.Reproduction studies have been performed in rats at doses up to 6.6 times the human dose and have revealed no evidence of harm to the fetus caused by lidocaine. There are, however, no adequate and well-controlled studies in pregnant women. Animal reproduction studies are not always predictive of human response. General consideration should be given to this fact before administering lidocaine to women of childbearing potential, especially during early pregnancy when maximum organogenesis takes place.

Labor and Delivery

Lidocaine is not contraindicated in labor and delivery. Should Lidocaine Ointment 5% be used concomitantly with other products containing lidocaine, the total dose contributed by all formulations must be kept in mind.

Nursing Mothers

It is not known whether this drug is excreted in human milk. Because many drugs are excreted in human milk, caution should be exercised when lidocaine is administered to a nursing woman.

Pediatric Use

Dosage in children should be reduced, commensurate with age, body weight and physical condition. Caution must be taken to avoid overdosage when applying Lidocaine Ointment 5% to large areas of injured or abraded skin, since the systemic absorption of lidocaine may be increased under such conditions (see DOSAGE AND ADMINISTRATION) .

ADVERSE REACTIONS

Adverse experiences following the administration of lidocaine are similar in nature to those observed with other amide local anesthetic agents. These adverse experiences are, in general, dose-related and may result from high plasma levels caused by excessive dosage or rapid absorption, or may result from a hypersensitivity, idiosyncrasy or diminished tolerance on the part of the patient. Serious adverse experiences are generally systemic in nature. The following types are those most commonly reported:

Central nervous system

CNS manifestations are excitatory and/or depressant and may be characterized by lightheadedness, nervousness, apprehension, euphoria, confusion, dizziness, drowsiness, tinnitus, blurred or double vision, vomiting, sensations of heat, cold or numbness, twitching, tremors, convulsions, unconsciousness, respiratory depression and arrest. The excitatory manifestations may be very brief or may not occur at all, in which case the first manifestation of toxicity may be drowsiness merging into unconsciousness and respiratory arrest. Drowsiness following the administration of lidocaine is usually an early sign of a high blood level of the drug and may occur as a consequence of rapid absorption.

Cardiovascular system

Cardiovascular manifestations are usually depressant and are characterized by bradycardia, hypotension, and cardiovascular collapse, which may lead to cardiac arrest.

Allergic

Allergic reactions are characterized by cutaneous lesions, urticaria, edema or anaphylactoid reactions. Allergic reactions may occur as a result of sensitivity either to the local anesthetic agent or to other components in the formulation. Allergic reactions as a result of sensitivity to lidocaine are extremely rare and, if they occur, should be managed by conventional means. The detection of sensitivity by skin testing is of doubtful value.

To report SUSPECTED ADVERSE REACTIONS, contact Amneal Pharmaceuticals at 1-877-835-5472 or FDA at 1-800-FDA-1088 orwww.fda.gov/medwatch.

OVERDOSAGE

Acute emergencies from local anesthetics are generally related to high plasma levels encountered during therapeutic use of local anesthetics (see ADVERSE REACTIONS, WARNINGS, and PRECAUTIONS).

Management of local anesthetic emergencies

The first consideration is prevention, best accomplished by careful and constant monitoring of cardiovascular and respiratory vital signs and the patient's state of consciousness after each local anesthetic administration. At the first sign of change, oxygen should be administered.

The first step in the management of convulsions consists of immediate attention to the maintenance of a patent airway and assisted or controlled ventilation with oxygen and a delivery system capable of permitting immediate positive airway pressure by mask. Immediately after the institution of these ventilatory measures, the adequacy of the circulation should be evaluated, keeping in mind that drugs used to treat convulsions sometimes depress the circulation when administered intravenously. Should convulsions persist despite adequate respiratory support, and if the status of the circulation permits, small increments of an ultra-short acting barbiturate (such as thiopental or thiamylal) or a benzodiazepine (such as diazepam) may be administered intravenously. The clinician should be familiar, prior to use of local anesthetics, with these anticonvulsant drugs. Supportive treatment of circulatory depression may require administration of intravenous fluids and, when appropriate, a vasopressor as directed by the clinical situation (e.g., ephedrine).

If not treated immediately, both convulsions and cardiovascular depression can result in hypoxia, acidosis, bradycardia, arrhythmias and cardiac arrest. If cardiac arrest should occur, standard cardiopulmonary resuscitative measures should be instituted.

Dialysis is of negligible value in the treatment of acute overdosage with lidocaine.

The oral LD50of lidocaine HCI in non-fasted female rats is 459 (346 to 773) mg/kg (as the salt) and 214 (159 to 324) mg/kg (as the salt) in fasted female rats.

DOSAGE AND ADMINISTRATION

When Lidocaine Ointment 5% is used concomitantly with other products containing lidocaine, the total dose contributed by all formulations must be kept in mind.

Adult

A single application should not exceed 5 g of Lidocaine Ointment 5%, containing 250 mg of lidocaine base (equivalent chemically to approximately 300 mg of lidocaine hydrochloride). This is roughly equivalent to squeezing a six (6) inch length of ointment from the tube. In a 70 kg adult this dose equals 3.6 mg/kg (1.6 mg/lb) lidocaine base. No more than one-half tube, approximately 17 g to 20 g of ointment or 850 mg to 1000 mg lidocaine base, should be administered in any one day.

Although the incidence of adverse effects with Lidocaine Ointment 5% is quite low, caution should be exercised, particularly when employing large amounts, since the incidence of adverse effects is directly proportional to the total dose of local anesthetic agent administered.

Dosage for children

It is difficult to recommend a maximum dose of any drug for children since this varies as a function of age and weight. For children less than ten years who have a normal lean body mass and a normal lean body development, the maximum dose may be determined by the application of one of the standard pediatric drug formulas (e.g., Clark's rule). For example a child of five years weighing 50 lbs., the dose of lidocaine should not exceed 75 mg to 100 mg when calculated according to Clark's rule. In any case, the maximum amount of lidocaine administered should not exceed 4.5 mg/kg (2 mg/lb) of body weight.

Administration

For medical use, apply topically for adequate control of symptoms. The use of a sterile gauze pad is suggested for application to broken skin tissue. Apply to the tube prior to intubation.

In dentistry, apply to previously dried oral mucosa. Subsequent removal of excess saliva with cotton rolls or saliva ejector minimizes dilution of the ointment, permits maximum penetration, and minimizes the possibility of swallowing the topical ointment.

For use in connection with the insertion of new dentures, apply to all denture surfaces contacting mucosa.

IMPORTANT: Patients should consult a dentist at intervals not exceeding 48 hours throughout the fitting period.

HOW SUPPLIED

Lidocaine Ointment USP, 5%is supplied as a white to off-white color ointment.

It is available as follows:
35.44 g (1 ¼ oz) laminate tubes with a child-resistant cap, NDC 85509-1918-3.

50 g (1 ¾ oz) double wall jar, with a child-resistant cap, NDC 85509-1918-1.

50 g (1 ¾ oz) double wall jar, with a child-resistant cap, NDC 85509-1918-5.
Pharmacist:If dispensed to a consumer, provide child resistant package for dispensing.

Store at 20° to 25°C (68° to 77°F); excursions permitted between 15° to 30°C (59° to 86°F) [see USP Controlled Room Temperature].

Distributed by:

Amneal Pharmaceuticals LLC

Bridgewater, NJ 08807

Rev. 10-2018-08

Repackaged/Relabeled by:
PHOENIX RX LLC
Hatboro, PA 19040